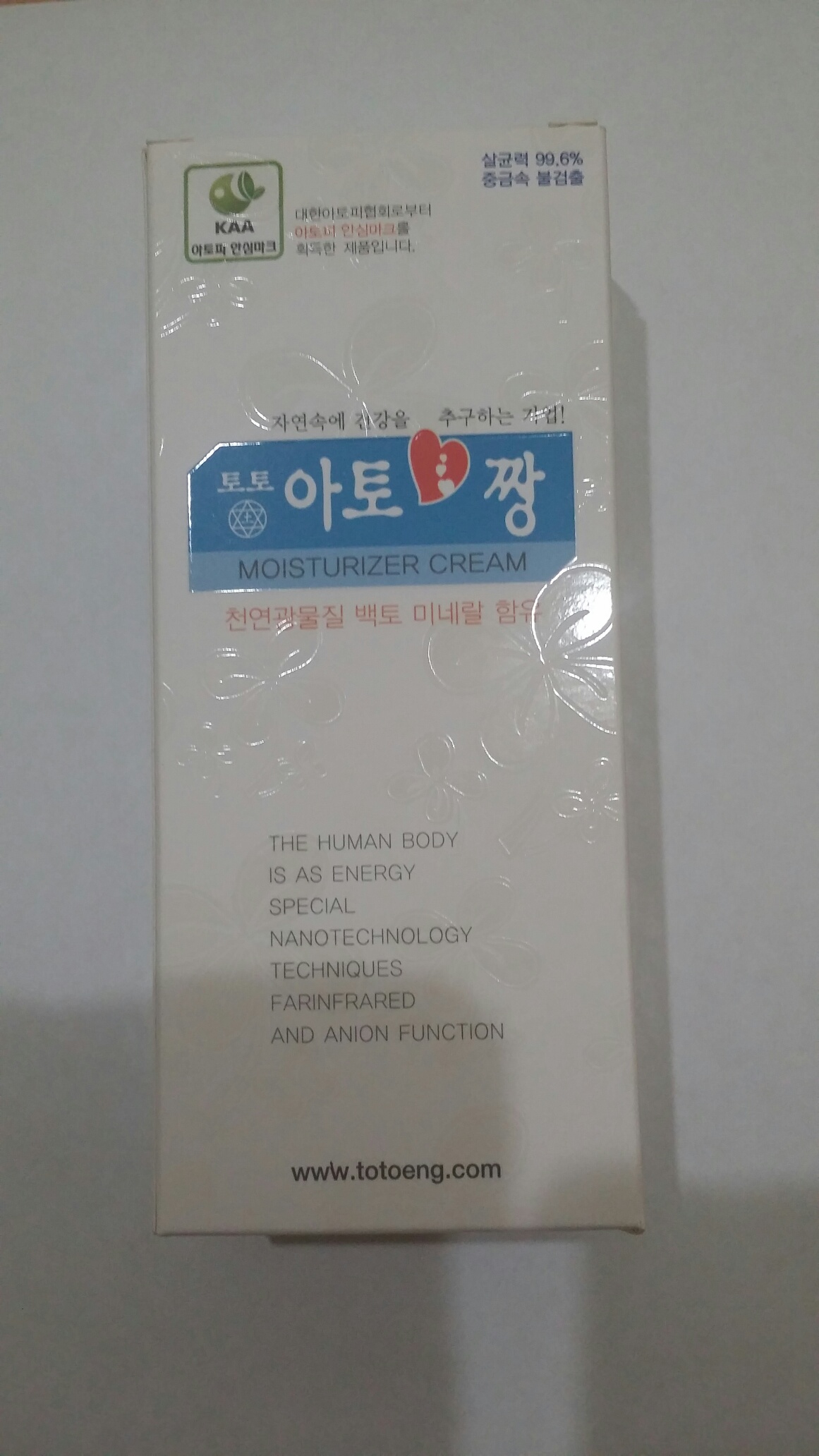 DRUG LABEL: Nature and Health Beauty (Moisturizing Cream, Whitening Cream)
NDC: 69741-1001 | Form: CREAM
Manufacturer: Nature and Health Beauty Co., Ltd.
Category: otc | Type: HUMAN OTC DRUG LABEL
Date: 20150416

ACTIVE INGREDIENTS: MINERAL OIL 1.2 g/120 g; GLYCERIN 1.2 g/120 g
INACTIVE INGREDIENTS: WATER; 1,3-BUTYLENE GLYCOL; CALCIUM SULFATE DIHYDRATE; BASSIA SCOPARIA FRUIT; HYALURONATE SODIUM; MACADAMIA SEED OIL GLYCERETH-8 ESTERS; POLYGLYCERYL-3 DIOLEATE; ALOE VERA LEAF; SQUALENE; UREA

ACTIVE INGREDIENTS

Mineral Oil 1%, Glycerin 1%

PURPOSE

Skin Protectant

KEEP OUT OF REACH OF CHILDREN

USES

To help the treatment of atopy, pruritus senilis, psoriasis and sensitive dermatitis.

WARNING

For external use only. Do not swallow.

If you take any serious medications or medical condition, consult your doctor.

DIRECTION

Apply to affected area twice daily, morning and evening. Gently massage onto damp skin after washing face or stepping out of the shower or bath.

INACTIVE INGREDIENT

Purified Water, Butylene Glycol, Squalene, White Clay (terra alba), Urea, Kochia Scoparia Fruit Extract, Sodium Hyaluronate, Macadamia Seed Oil, Polyglyceryl-3, Methyl Glucose Dioleate, Aloe Vera Leaf Juice, Sorbitan Sterate, Dimethicone 6, Beewax, Camelia Oil, Simmondsia Chinensis (jojoba) Seed Oil, Centella Extract, Plantago Extract, Portulaca Extract, Japanese Angelica Root Extract, Trehalose, Malt Extract, Propolis Extract, Polyacrylamide, C13-14 Iosparaffin, Laureth-7, Salicylic Acid, Allantoin, Polyglutamic Acid, Methyl Paraben, Ceramide3, Phenoxyethanol, Propylparaben, Disodium EDTA, Fragrance.

OTHER INFORMATION

- Keep product out of direct sunlight, high temperature and humidity.
- Store in a cool dry place.
- Be careful not to get it in your eyes.
- If rashes or skin irritation occurs, discontinue use.
- Any items past the expiration date or damaged in transit can be exchanged where you originally purchased the item.

SPL UNCLASSIFIED SECTION

Do not exceed the recommended dosage.

To assure freshness and potency, store at room temperature 15oC - 30oC.

Store away from heat, light and moisture, if you are pregnant, nursing, taking any medication or have a medical condition, please consult your healthcare practitioner.